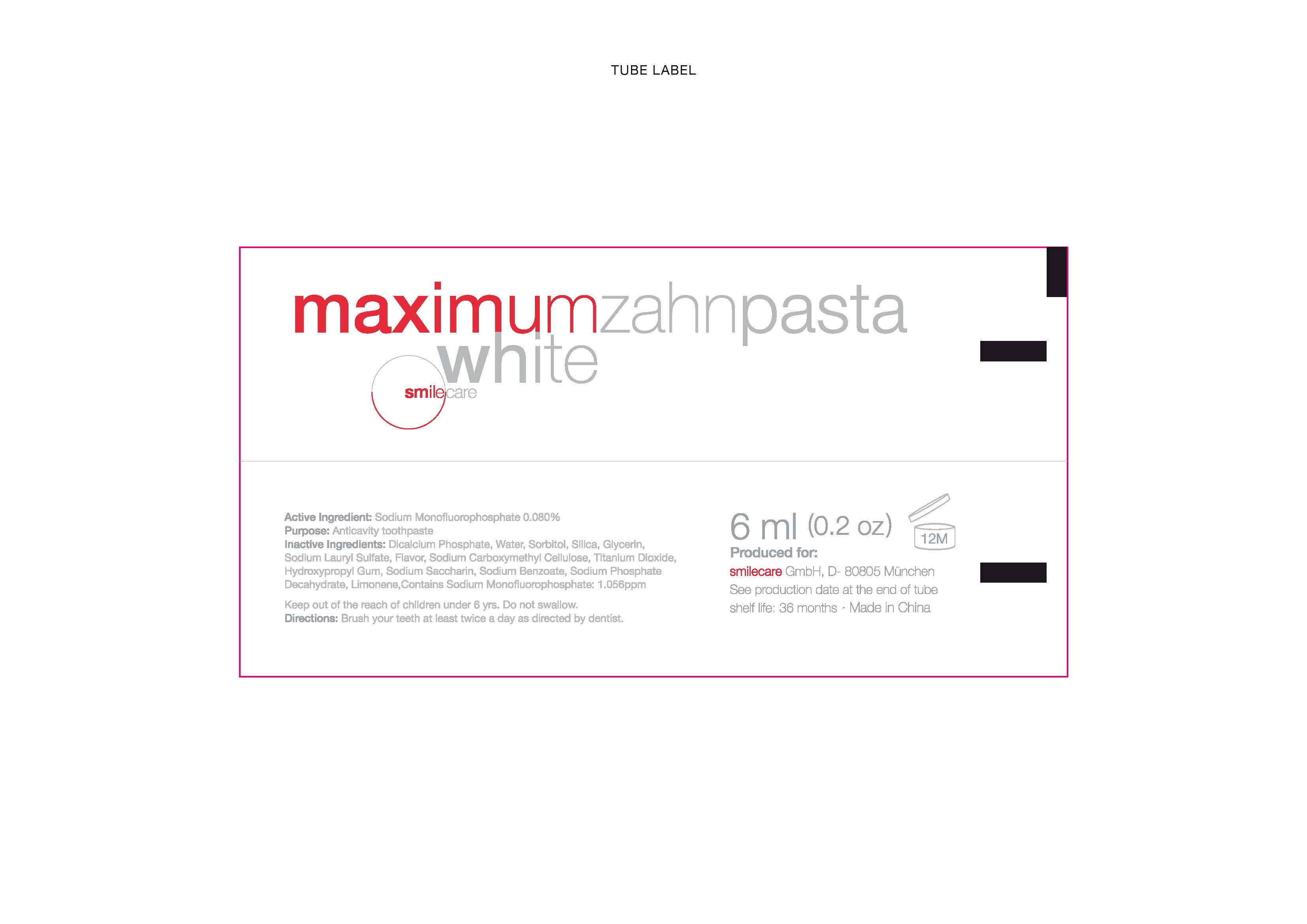 DRUG LABEL: smilecare
                
NDC: 69108-001 | Form: PASTE, DENTIFRICE
Manufacturer: Shantou MContinents Trading Co, LTD
Category: otc | Type: HUMAN OTC DRUG LABEL
Date: 20140714

ACTIVE INGREDIENTS: SODIUM MONOFLUOROPHOSPHATE 64 mg/8 g
INACTIVE INGREDIENTS: CALCIUM PHOSPHATE, DIBASIC, ANHYDROUS; WATER; SORBITOL; SILICON DIOXIDE; GLYCERIN; SODIUM LAURYL SULFATE; CARBOXYMETHYLCELLULOSE SODIUM; TITANIUM DIOXIDE; HYDROXYPROPYL CELLULOSE (TYPE H); SACCHARIN SODIUM; SODIUM BENZOATE; SODIUM PHOSPHATE, DIBASIC, DODECAHYDRATE; LIMONENE, (+/-)-

Drug Facts

INACTIVE INGREDIENT

Inactive Ingredients: Dicalcium Phosphate, Water, Sorbitol, Silica, Glycerin,

Sodium Lauryl Sulfate, Flavor, Sodium Carboxymethyl Cellulose, Titanium Dioxide,

Hydroxypropyl Gum, Sodium Saccharine, Sodium Benzoate, Sodium Phosphate

Decahydrate, Limonene, Contains Sodium Monoflourophosphate: 1.0556ppm

Active Ingredient: Sodium Monofluorophosphate 0.080 %

Purpose: Anticavity toothpaste

Keep out of reach of children under 6 yrs.

WARNINGS

Do not swallow

DOSAGE AND ADMINISTRATION

Directions: Brush your teeth at least twice a day as directed by dentist.

INDICATIONS AND USAGE

Anticavity toothpaste